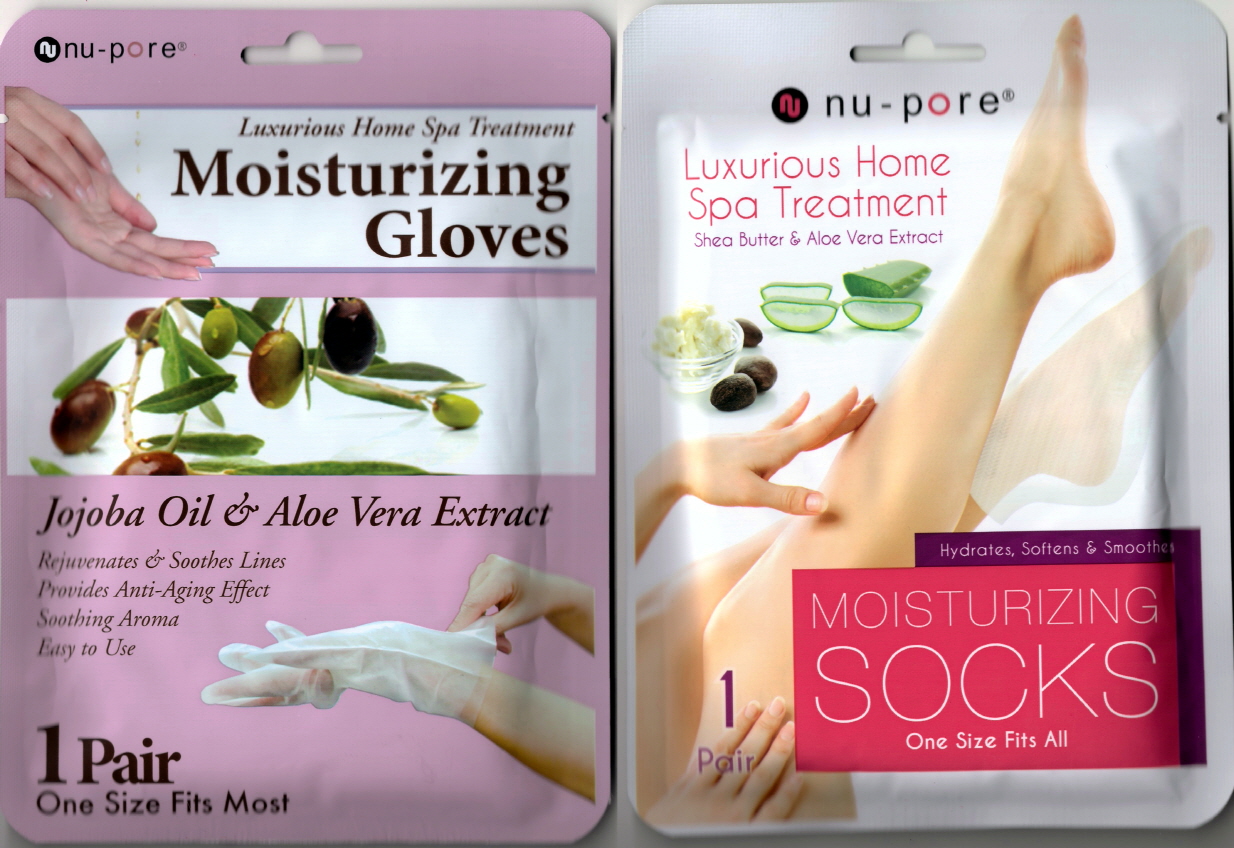 DRUG LABEL: Mousturizing Gloves and Socks
NDC: 71149-0001 | Form: LIQUID
Manufacturer: Clean Sense
Category: otc | Type: HUMAN OTC DRUG LABEL
Date: 20161228

ACTIVE INGREDIENTS: JOJOBA OIL 0.01 g/100 g; ALOE VERA LEAF 1 g/100 g; SHEA BUTTER 3.5 g/100 g
INACTIVE INGREDIENTS: WATER; BUTYLENE GLYCOL; UREA; GLYCERIN

Drug Facts

ACTIVE INGREDIENT

Butyrospermum Parkii(Shea Butter), Aloe Barbadensis Leaf Extract, Simmondsia Chinensis (Jojoba) Seed Oil

INACTIVE INGREDIENT

Water, Glycerin, Butylene Glycol, Urea, Betaine, Collagen, Etc.

PURPOSE

Skin protectant

keep out of reach of the children

WARNINGS

1. If the following symptoms occur after product use, stop using the product immediately and consult a dermatologist (continuous use can exacerbate the symptoms).
1) Occurrence of red spots, swelling, itchiness, and other skin irritation
2) If the symptoms above occur after the application area is exposed to direct sunlight
2. Do not use on open wounds, eczema, and other skin irritations
3. Precaution for Storage and Handling
1) Close the lid after use
2) Keep out of reach of infants and children
3) Do not to store in a place with high/low temperature and exposed to direct sunlight

4. Use as avoiding eye areas.

DOSAGE AND ADMINISTRATION

for external use only

INDICATIONS AND USAGE

Moisturizing Socks
1. Rinse feet thoroughly and completely dry them to remove any moisture.
2. Insert feet in the moisturizing socks and make sure the contents of the liquid are inside.
3. While wearing the moisturizing socks, massage feet to absorb all the liquid.
4. After 20 to 30 minutes, remove moisturizing socks and massage in the remaining liquid for long-lasting hydration.
Moisturizing Gloves
1. Wash hands thoroughly and completely dry them to remove any moisture.
2. Open and put hands in the hand moisturizing treatment and make sure the contents of the liquid makeup is inside.
3. While wearing the hand moisturizing treatment, massage them to thoroughly absorb all the moisture.
4. After 20-30 minutes remove the hand moisturizing treatment and softly pat down the remaining contents for better absorption.